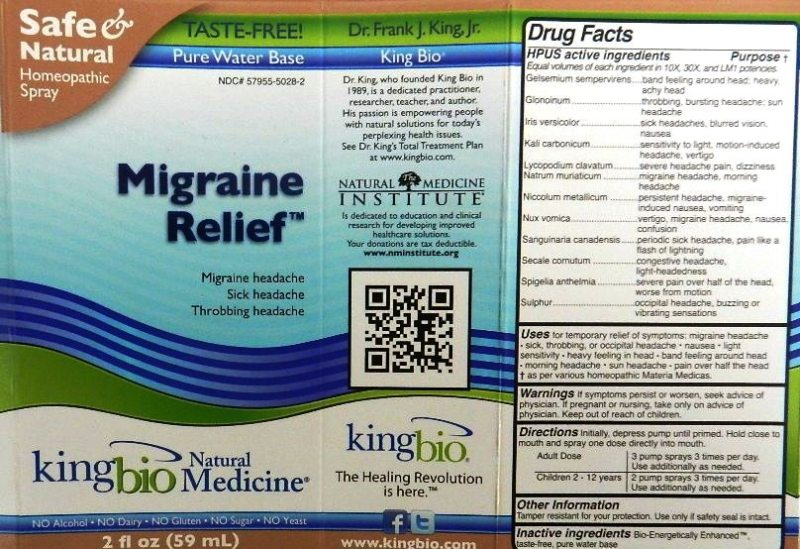 DRUG LABEL: Migraine Relief
NDC: 57955-5028 | Form: LIQUID
Manufacturer: King Bio Inc.
Category: homeopathic | Type: HUMAN OTC DRUG LABEL
Date: 20120220

ACTIVE INGREDIENTS: GELSEMIUM SEMPERVIRENS ROOT 10 [hp_X]/59 mL; NITROGLYCERIN 10 [hp_X]/59 mL; IRIS VERSICOLOR ROOT 10 [hp_X]/59 mL; POTASSIUM CARBONATE 10 [hp_X]/59 mL; LYCOPODIUM CLAVATUM SPORE 10 [hp_X]/59 mL; SODIUM CHLORIDE 10 [hp_X]/59 mL; NICKEL 10 [hp_X]/59 mL; STRYCHNOS NUX-VOMICA SEED 10 [hp_X]/59 mL; SANGUINARIA CANADENSIS ROOT 10 [hp_X]/59 mL; CLAVICEPS PURPUREA SCLEROTIUM 10 [hp_X]/59 mL; SPIGELIA ANTHELMIA 10 [hp_X]/59 mL; SULFUR 10 [hp_X]/59 mL
INACTIVE INGREDIENTS: WATER

Migraine Relief

Active Ingredients

HPUS active Ingredients

Equal volmes of each ingredient in 10X, 30X and LM1 potencies.

Gelsemium sempervirens

Glonoinum

Iris versicolor

Kali carbonicum

Lycopodium clavatum

Natrum muriaticum

Niccolum metallicum

Nux vomica

Sanguinaria canadensis

Secale cornutum

Spigelia anthelmia

Sulphur

Reference image of migraine relief.jpg

Inactive Ingredient

Bio-Energetically Enhanced taste-free, pure water base.

Reference image migraine relief.jpg

Dosage and Administration

Directions Initially, depress pump until primed. Hold close to mouth and spray one dose directly into mouth.

Adult Dose 3 pump sprays 3 times per day. Use additionally as needed.

Children 2-12 years 2 pump sprays 3 times per day. Use additionally as needed.

Reference image of migraine relief.jpg

Purpose

HPUS active ingredients Purpose

Equal volmes of each ingredient in 10X, 30X and LM1 potencies.

Gelsemium sempervirens.....................................band feeling around head, heavy, achy head

Glonoinum...........................................................throbbing, bursting headache; sun headache

Iris versicolor......................................................sick headaches, blurred vision, nausea

Kali carbonicum...................................................sensitivity to light, motion-induced headache, vertigo

Lycopodium clavatum..........................................severe headache pain, dizziness

Natrum muriaticum..............................................migraine headache, morning headache

Niccolum metallicum............................................persistent headache, migraine-induced nausea, vomiting

Nux vomica.........................................................vertigo, migraine headache, nausea, confusion

Sanguinaria canadensis.......................................periodic sick headache, pain like a flash of lightning

Secale cornutum.................................................congestive headache, light-headedness

Spigelia anthelmia...............................................severe pain over half of the head, worse from motion

Sulphur.............................................................. occipital headache, buzzing or vibrating sensations

Reference image of migraine relief.jpg

Warning Section

Warning: If symptoms persist or worsen, seek advice of physician. If pregnant or nursing, take only on advice of a physician.

Other Information: Tamper resistant for your protection. Use only if safety seal is intact.

Reference image of migraine relief.jpg

Keep out of reach of children.

Reference image of migraine relief.jpg

Indications and usage

Uses for temporary relief of symptoms:

- migraine headache
- sick, throbbing, or occipital headache
- nausea
- light sensitivity
- heavy feeling in head
- band feeling around head
- morning headache
- sun headache
- pain over half the head

as per various homeopathic Materia Medicas.
Reference image of migraine relief.jpg

PACKAGE LABEL

King Bio Inc.

3 Westside Drive

Asheville NC 28806

Questions? Call 800.543.3245

www.kingbio.com

Safe and Natural Homeopathic Spray